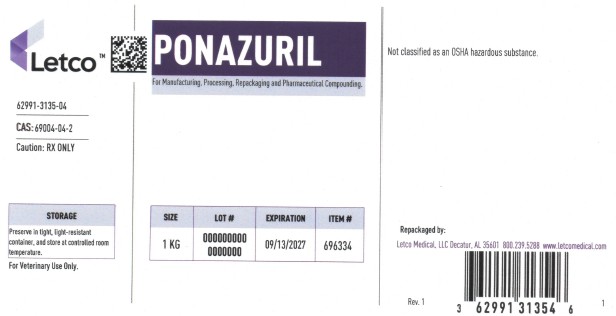 DRUG LABEL: Ponazuril
NDC: 62991-3135 | Form: POWDER
Manufacturer: LETCO MEDICAL, LLC
Category: other | Type: BULK INGREDIENT - ANIMAL DRUG
Date: 20250925

ACTIVE INGREDIENTS: PONAZURIL 1 g/1 g

Ponazuril

PACKAGE LABEL

Ponazuril 1kg